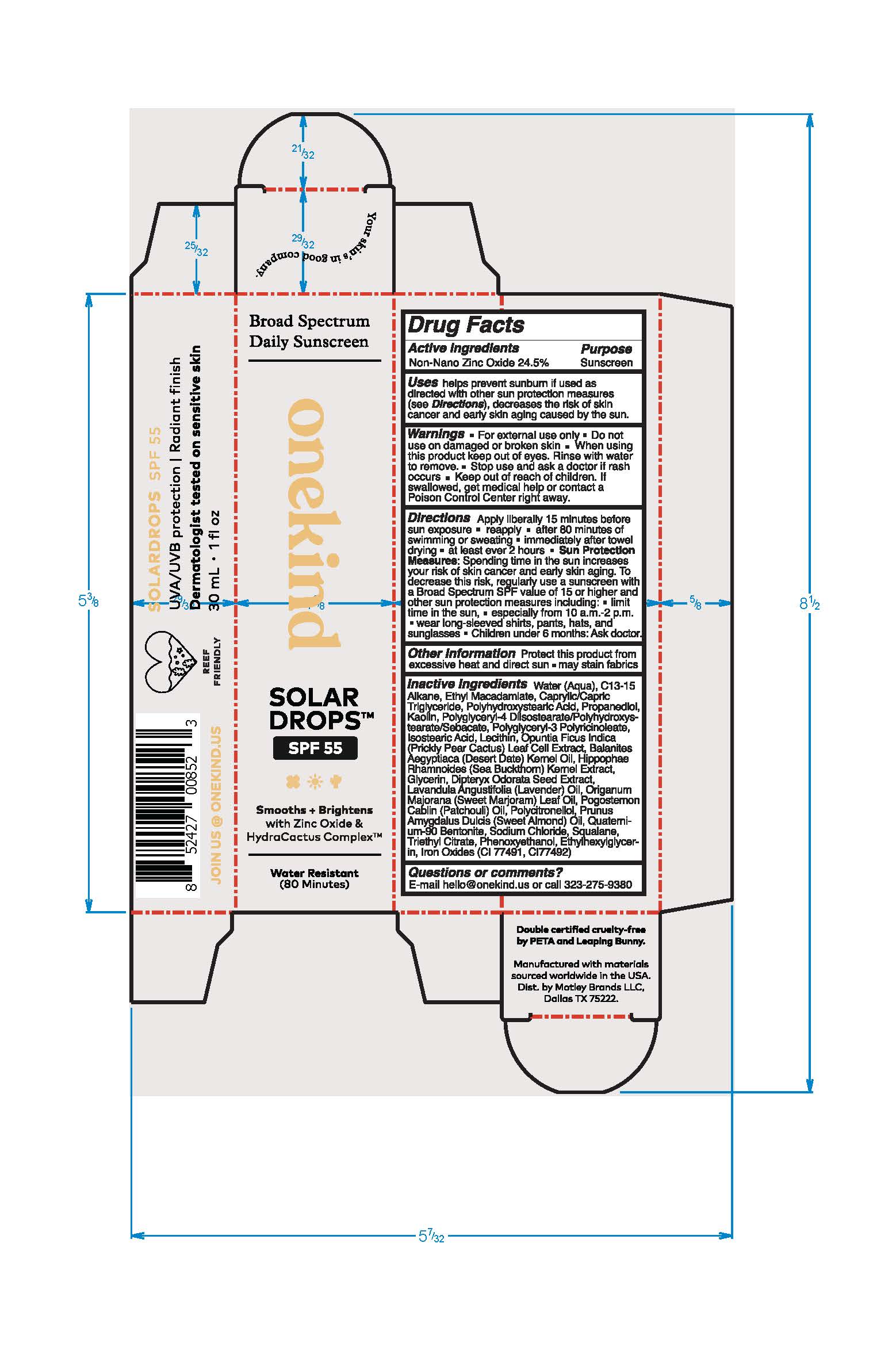 DRUG LABEL: Daily Broad Spectrum Serum Solardrops
NDC: 83260-100 | Form: LOTION
Manufacturer: Motley Brands LLC
Category: otc | Type: HUMAN OTC DRUG LABEL
Date: 20251229

ACTIVE INGREDIENTS: ZINC OXIDE 245 mg/1 g
INACTIVE INGREDIENTS: TRIETHYL CITRATE; ETHYLHEXYLGLYCERIN; POLYGLYCERYL-3 PENTARICINOLEATE; MEDIUM-CHAIN TRIGLYCERIDES; POLYHYDROXYSTEARIC ACID (2300 MW); KAOLIN; HIPPOPHAE RHAMNOIDES SEED; POLYGLYCERYL-4 DIISOSTEARATE/POLYHYDROXYSTEARATE/SEBACATE; C13-15 ALKANE; PROPANEDIOL; .BETA.-CITRONELLOL, (R)-; BENTONITE; ETHYL MACADAMIATE; SWEET MARJORAM OIL; POGOSTEMON CABLIN LEAF OIL; ISOSTEARIC ACID; PHENOXYETHANOL; SODIUM CHLORIDE; FERRIC OXIDE RED; WATER; LAVENDER OIL; SQUALANE; OPUNTIA FICUS-INDICA LEAF; ALMOND OIL; LECITHIN, SUNFLOWER; DIPTERYX ODORATA SEED; DESERT DATE

Daily Broad Spectrum Serum Solardrops

Active Ingredients

Non-Nano Zinc Oxide 24.5%

Purpose

Sunscreen

Uses

helps prevent sunburn if used as directed with other sun protection measures (see Directions), decreases the risk of skin cancer and early skin aging caused by the sun.

Warnings

• For external use only

• Do not use on damaged or broken skin

• When using this product keep out of eyes. Rinse with water to remove.

• Stop use and ask a doctor if rash occurs

• Keep out of reach of children. If swallowed, get medical help or contact a Poison Control Center right away.

Directions

Apply liberally 15 minutes before sun exposure
• reapply • after 80 minutes of swimming or sweating • immediately after towel drying • at least ever 2 hours
• Sun Protection Measures: Spending time in the sun increases your risk of skin cancer and early skin aging. To decrease this risk, regularly use a sunscreen with a Broad Spectrum SPF value of 15 or higher and other sun protection measures including:
• limit time in the sun, especially from 10 a.m.-2 p.m.
• wear long-sleeved shirts, pants, hats, and sunglasses
• Children under 6 months: Ask doctor

Other Information

Protect this product from excessive heat and direct sun
■ may stain fabrics

Inactive Ingredients

Water (Aqua), C13-15 Alkane, Ethyl Macadamiate, Caprylic/Capric Triglyceride, Polyhydroxystearic Acid, Propanediol, Kaolin, Polyglyceryl-4 Diisostearate/Polyhydroxystearate/Sebacate, Polyglyceryl-3 Polyricinoleate, Isostearic Acid, Lecithin, Opuntia Ficus-Indica (Prickly Pear Cactus) Leaf Cell Extract, Balanites Aegyptiaca (Desert Date) Kernel Oil, Hippophae Rhamnoides (Sea Buckthorn) Kernel Extract, Dipteryx Odorata, Lavandula Angustifolia (Lavender) Oil, Origanum Majorana (Sweet Marjoram) Leaf Oil, Pogostemon Cablin (Patchouli) Oil, Polycitronellol, Prunus Amygdalus Dulcis (Sweet Almond) Oil, Polyquaternium-90, Bentonite, Sodium Chloride, Squalane, Triethyl Citrate, Phenoxyethanol, Ethylhexylglycerin, Iron Oxides (CI 77491, CI 77492)

Questions?

E-mail hello@onekind.us or call 323-275-9380